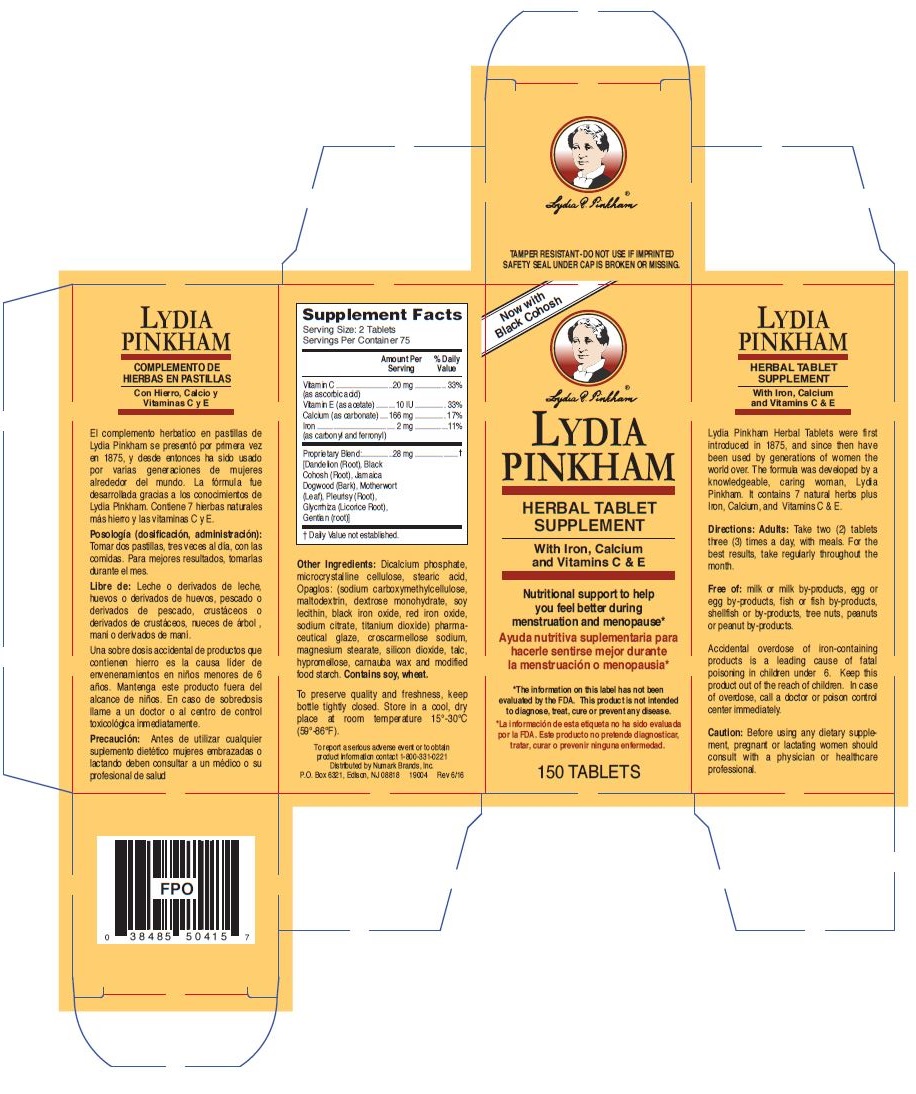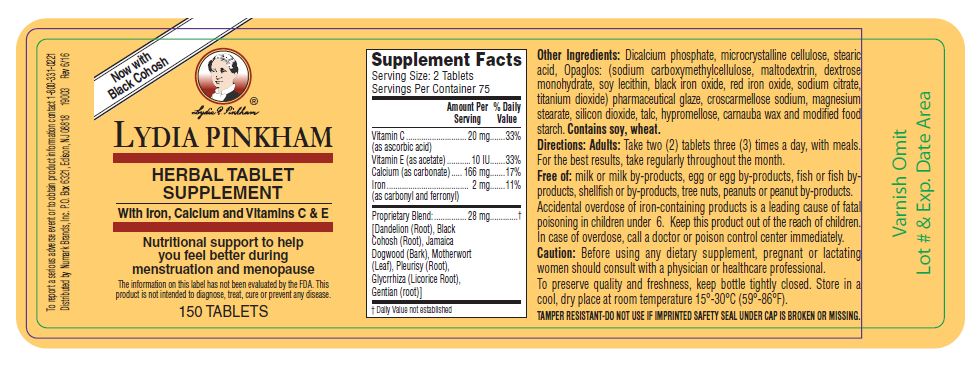 DRUG LABEL: LYDIA PINKHAM Herbal Supplement 
NDC: 69846-504 | Form: TABLET
Manufacturer: NUMARK BRANDS, INC
Category: other | Type: DIETARY SUPPLEMENT
Date: 20160812

ACTIVE INGREDIENTS: Ascorbic Acid 10 mg/1 1; .alpha.-tocopherol Acetate, Dl- 4.5 mg/1 1; Calcium Carbonate 83 mg/1 1; Iron 1 mg/1 1
INACTIVE INGREDIENTS: Taraxacum Officinale Root; Black Cohosh; Piscidia Piscipula Root Bark; Leonurus Cardiaca; Asclepias Tuberosa Root; Gentiana Lutea Root; Calcium Phosphate, Dibasic, Anhydrous; Cellulose, Microcrystalline; Stearic Acid; Carboxymethylcellulose Sodium; Maltodextrin; Dextrose Monohydrate; Lecithin, Soybean; Ferrosoferric Oxide; Ferric Oxide Red; Sodium Citrate; Titanium Dioxide; Shellac; Croscarmellose Sodium; Magnesium Stearate; Silicon Dioxide; Talc; Hypromelloses; Carnauba Wax; Starch, Wheat

LYDIA PINKHAM HERBAL TABLET SUPPLEMENT With Iron, Calcium and Vitamins C & E
LYDIA PINKHAM COMPLEMENTO DE HIERBAS EN PASTILLAS Con Hierro, Calcio y Vitaminas C y E

Supplement Facts

Serving Size: 2 tablets
Servings Per Container 75

Amount Per Serving |  | % Daily Value
Vitamin C (as ascorbic acid) | 20 mg | 33%
Vitamin E (as acetate) | 10 IU | 33%
Calcium (as carbonate) | 166 mg | 17%
Iron (as carbonyl and ferronyl) | 2 g | 11%
Proprietary blend | 28 g | †
Dandelion (Root) |  | †
Black Cohosh (Root) |  | †
Jamaica Dogwood (Bark) |  | †
Motherwort (Leaf) |  | †
Pleurisy (Root) |  | †
Glycrrhiza (Licorice Root) |  | †
Gentian (root) |  | †
† Daily Value not established

Other Ingredients: Dicalcium phosphate, microcrystalline cellulose, stearic acid, Opaglos: (sodium carboxymethylcellulose, maltodextrin, dextrose monohydrate, soy lecithin, black iron oxide, red iron oxide, sodium citrate, titanium dioxide) pharmaceutical glaze, croscarmellose sodium, magnesium stearate, silicon dioxide, talc, hypromellose, carnauba wax and modified food starch. Contains soy, wheat.

Free of: milk or milk by-products, egg or egg by-products, fish or fish by-products, shellfish or by-products, tree nuts, peanuts or peanut by-products.

Libre de: Leche o derivados de leche, huevos o derivados de huevos, pescado o derivados de pescado, crustáceos o derivados de crustáceos, nueces de árbol , maní o derivados de maní.

Directions:

Adults: Take two (2) tablets three (3) times a day, with meals. For the best results, take regularly throughout the month.

Posología, (dosificación, administración):

Tomar dos pastillas, tres veces al día, con las comidas. Para mejores resultados, tomarlas durante el mes.

PRECAUTIONS

Caution: Before using any dietary supplement, pregnant or lactating women should consult with a physician or healthcare professional.

PRECAUTIONS

Precaución: Antes de utilizar cualquier suplemento dietético mujeres embrazadas o lactando deben consultar a un médico o su profesional de salud

HEALTH CLAIM

Nutritional support to help you feel better during menstruation and menopause*

* The information on this label has not been evaluated by the FDA. This product is not intended to diagnose, treat, cure or prevent any disease.

Lydia Pinkham Herbal Tablets were first introduced in 1875, and since then have been used by generations of women the world over. The formula was developed by a knowledgeable, caring woman, Lydia Pinkham. It contains 7 natural herbs plus Iron, Calcium, and Vitamins C & E.

HEALTH CLAIM

Ayuda nutritiva suplementaria para hacerle sentirse mejor durante la menstruación o menopausia*

* La información de esta etiqueta no ha sido evaluada por la FDA. Este producto no pretende diagnosticar, tratar, curar o prevenir ninguna enfermedad.

El complemento herbatico en pastillas de Lydia Pinkham se presentó por primera vez en 1875, y desde entonces ha sido usado por varias generaciones de mujeres alrededor del mundo. La fórmula fue desarrollada gracias a los conocimientos de Lydia Pinkham. Contiene 7 hierbas naturales más hierro y las vitaminas C y E.

WARNINGS

Accidental overdose of iron-containing products is a leading cause of fatal poisoning in children under 6. Keep this product out of the reach of children. In case of overdose, call a doctor or poison control center immediately.

WARNINGS

Una sobre dosis accidental de productos que contienen hierro es la causa líder de envenenamientos en niños menores de 6 años. Mantenga este producto fuera del alcance de niños. En caso de sobredosis llame a un doctor o al centro de control toxicológica inmediatamente.

SAFE HANDLING WARNING

To preserve quality and freshness, keep bottle tightly closed. Store in a cool, dry place at room temperature 15°-30°C (59°-86°F).

PRINCIPAL DISPLAY PANEL

Now with Black Cohosh
LYDIA PINKHAM
HERBAL TABLET SUPPLEMENT
With Iron, Calcium and Vitamins C & E
COMPLEMENTO DE HIERBAS EN PASTILLAS
Con Hierro, Calcio y Vitaminas C y E
150 TABLETS
To report a serious adverse event or to obtain product information contact 1-800-331-0221
Distributed by Numark Brands, Inc.
P.O. Box 6321, Edison, NJ 08818 19004 Rev 6/16

Now with Black Cohosh
LYDIA PINKHAM
HERBAL TABLET SUPPLEMENT
With Iron, Calcium and Vitamins C & E
8 FL.OZ.
TAMPER RESISTANT-DO NOT USE IF IMPRINTED SAFETY SEAL UNDER CAP IS BROKEN OR MISSING.
To report a serious adverse event or to obtain product information contact 1-800-331-0221
Distributed by Numark Brands, Inc. P.O. Box 6321, Edison, NJ 08818
19003 Rev 6/16